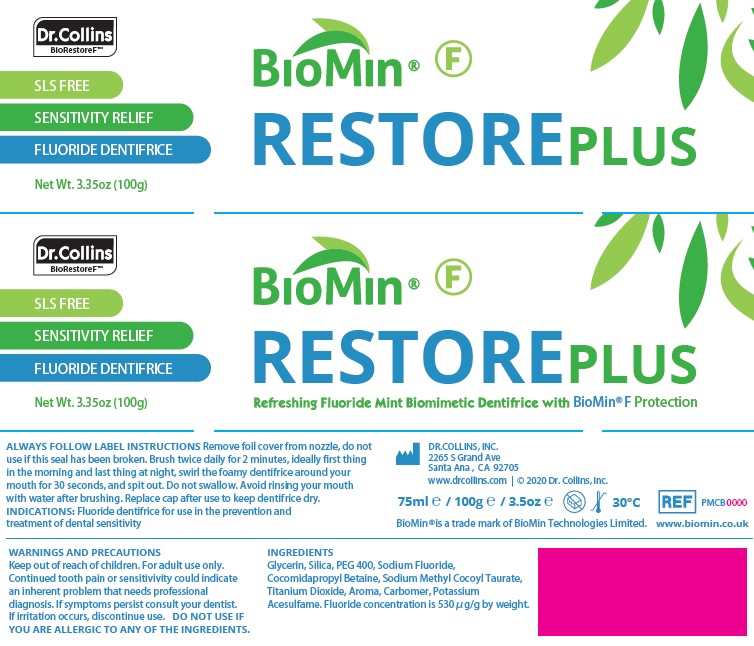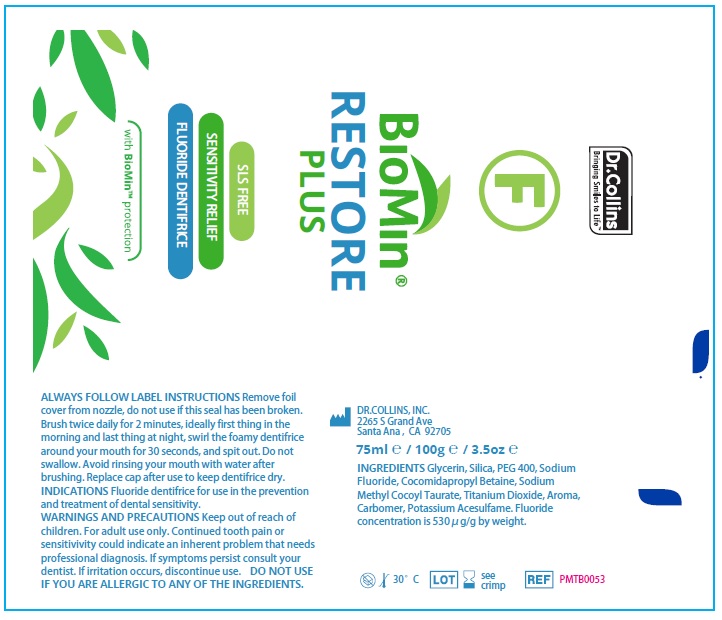 DRUG LABEL: Biomin Restore Plus
NDC: 77055-100 | Form: PASTE, DENTIFRICE
Manufacturer: DRCOLLINS, INC.
Category: otc | Type: HUMAN OTC DRUG LABEL
Date: 20200429

ACTIVE INGREDIENTS: SODIUM FLUORIDE 0.53 mg/1 g
INACTIVE INGREDIENTS: SODIUM METHYL COCOYL TAURATE 0.0055 g/1 g; GLYCERIN 0.573 g/1 g; COCAMIDOPROPYL BETAINE 0.0055 g/1 g; SILICON DIOXIDE 0.156 g/1 g; POLYETHYLENE GLYCOL 400 0.18 g/1 g; CARBOMER HOMOPOLYMER, UNSPECIFIED TYPE 0.0075 g/1 g; ACESULFAME POTASSIUM 0.004 g/1 g; TITANIUM DIOXIDE 0.01 g/1 g; PEPPERMINT 0.0085 g/1 g

BioMin Restore Plus

Purpose

Anticavity & Sensitivity Relief

Indications for Use

Fluoride dentifrice for use in the prevention and treatment of dental sensitivity.

Instructions for Use

Remove foil cover from nozzle, do not use if this seal has been broken. Brush twice daily for 2 minutes, ideally first thing in the morning and last thing at night, swirl the foamy dentifrice around your mouth for 30 seconds, and spit out. Do not swallow. Avoid rinsing your mouth
with water after brushing. Replace cap after use to keep dentifrice dry.

Warnings and Precautions

Continued tooth pain or sensitivivity could indicate an inherent problem that needs professional diagnosis. If symptoms persist consult your dentist. If irritation occurs, discontinue use.

Keep Out of Reach of Children. For Adults Use Only.

Warning

DO NOT USE IF YOU ARE ALLERGIC TO ANY OF THE INGREDIENTS

Active Ingredient

Sodium Fluoride. (Fluoride concentration is 530μg/g by weight.)

Inactive Ingredients

Glycerin, Silica, PEG 400, Cocomidapropyl Betaine, Sodium Methyl Cocoyl Taurate, Titanium Dioxide, Aroma, Carbomer, Potassium Acesulfame.

Dosage & Administration

Net Wt. 3.35oz (100g)

75ml e / 100g ℮ / 3.5oz ℮.

Storage & Handling

Storage temperatures limit: up to 30°C.

Do ot use if package is damaged.